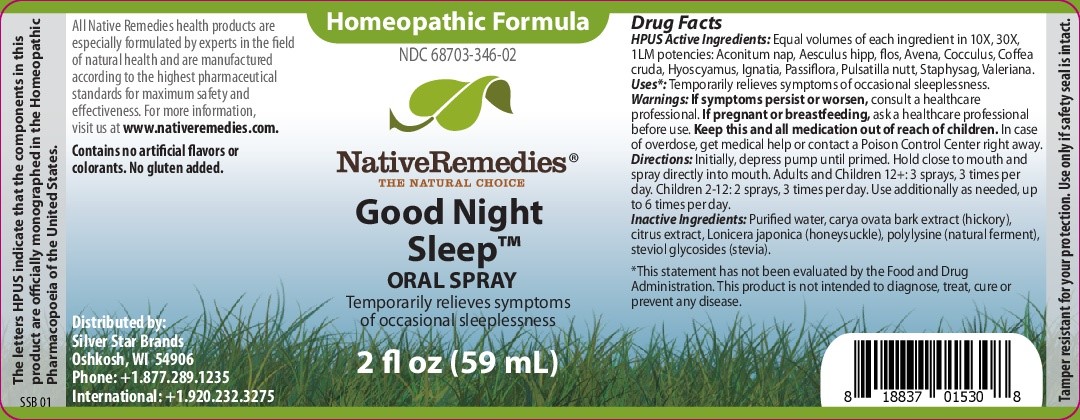 DRUG LABEL: Good Night Sleep
NDC: 68703-346 | Form: SPRAY
Manufacturer: Silver Star Brands
Category: homeopathic | Type: HUMAN OTC DRUG LABEL
Date: 20250101

ACTIVE INGREDIENTS: STRYCHNOS IGNATII WHOLE 10 [hp_X]/59 mL; COFFEA ARABICA FRUIT 10 [hp_X]/59 mL; ANEMONE PATENS WHOLE 10 [hp_X]/59 mL; VALERIANA OFFICINALIS WHOLE 10 [hp_X]/59 mL; AVENA SATIVA LEAF 10 [hp_X]/59 mL; PASSIFLORA INCARNATA FLOWER 10 [hp_X]/59 mL; ANAMIRTA COCCULUS SEED 10 [hp_X]/59 mL; DELPHINIUM STAPHISAGRIA SEED 10 [hp_X]/59 mL; ACONITUM NAPELLUS 10 [hp_X]/59 mL; AESCULUS HIPPOCASTANUM FLOWER 10 [hp_X]/59 mL; HYOSCYAMUS NIGER 10 [hp_X]/59 mL
INACTIVE INGREDIENTS: WATER; LONICERA JAPONICA FLOWER; CARYA OVATA BARK; GLUCOSYL STEVIOL; BENZYLPENICILLOYL POLYLYSINE; ANHYDROUS CITRIC ACID

NativeRemedies® Good Night Sleep Oral Spray

HPUS Active Ingredients: Equal volumes of each ingrediet in 10X, 30X, 1LM potencies. Aconitum nap, Aesculus hipp, flos, Avena, Cocculus, Coffea cruda, Hysocyamus, Ignatia, Passiflora, Pusatilla nutt, Staphysag, Valeriana.

Uses*

Uses*: Temporarily relieves symptoms of occasional sleeplessness.

*This statement has not been evaluated by the food and Drug Administration. This product is not inteded to diagnose, treat, cure or prevent any disease.

Warnings

If symptoms persist or worsen, consult a healthcare professional. If pregnant or breastfeeding, ask a healthcare professional before use. Keep this and all medication out of reach of children.

Directions

Initially, depress pump until primed. Hold close to mouth and spray directly into mouth. Adults and Children 12+: 3 sprays, 3 times per day. Children 2-12: 2 sprays, 3 times per day. Use additionally as needed, up to 6 times per day.

OTHER SAFETY INFORMATION

Contains no artificial flavors or colorants. No gluten added.

Tamper resistant for your protection. use only if saftey seal is intact.

Inactive Ingredients

Inactive Ingredients: Purified water, carya ovata bark extract (hickory), citrust extract, Lonicera japonica (honeysuckle), polylysine (natural ferment), steviol glycosides (stevia).

Inactive Ingredients

Inactive Ingredients: Purified water, carya ovata bark extract (hickory), citrust extract, Lonicera japonica (honeysuckle), polylysine (natural ferment), steviol glycosides (stevia).

KEEP OUT OF REACH OF CHILDREN

Keep this and all medication out of reach of children.

PREGNANCY OR BREAST FEEDING

If pregnant or breastfeeding, ask a healthcare professional before use.

PURPOSE

Temporarily relieves symptoms of occasional sleeplessness